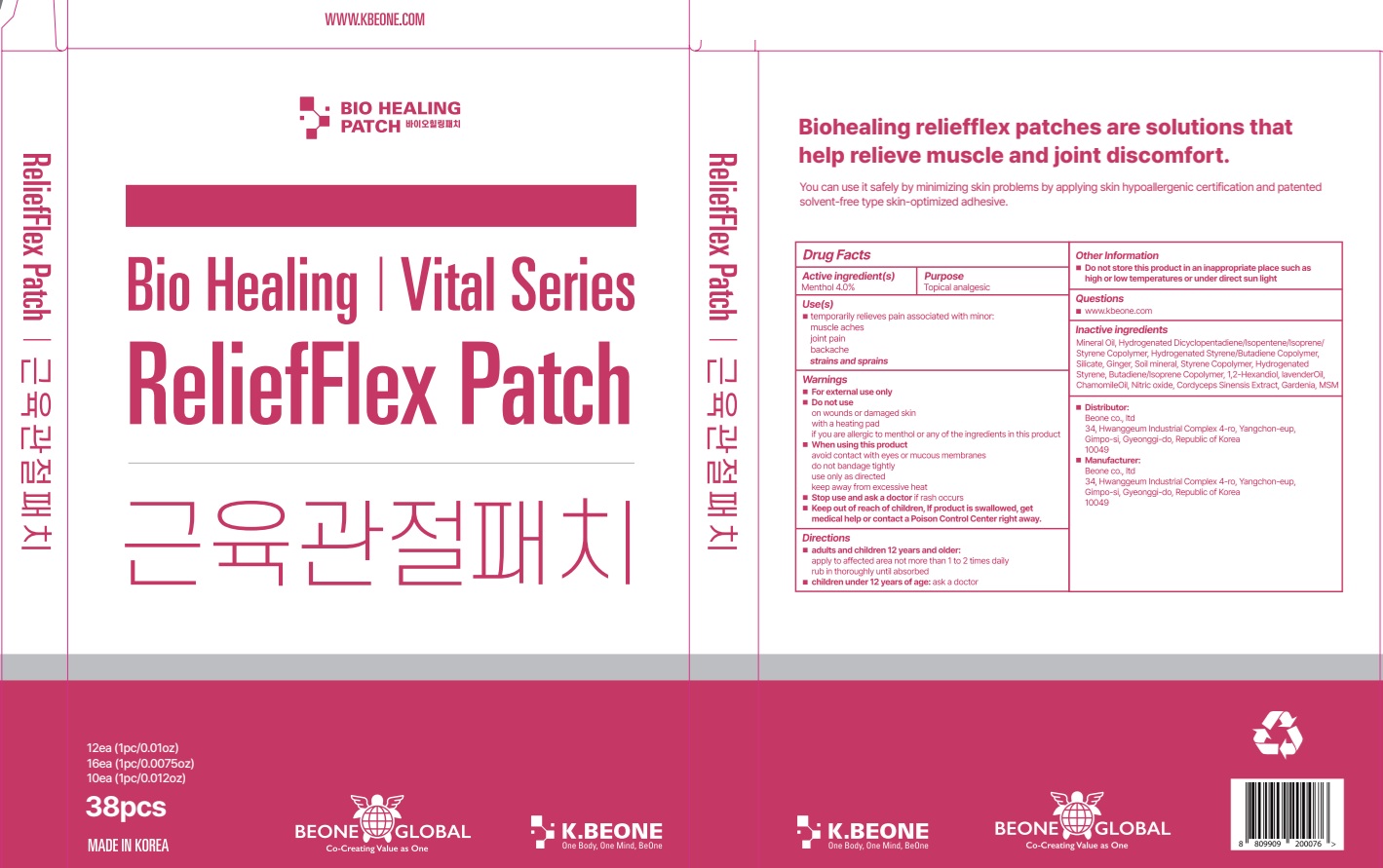 DRUG LABEL: Relief Flex
NDC: 87379-010 | Form: PATCH
Manufacturer: Beone Co., Ltd.
Category: otc | Type: HUMAN OTC DRUG LABEL
Date: 20260203

ACTIVE INGREDIENTS: MENTHOL 4 g/100 g
INACTIVE INGREDIENTS: MINERAL OIL; STYRENE; OPHIOCORDYCEPS SINENSIS; DIMETHYL SULFONE; LAVENDER OIL; CHAMOMILE FLOWER OIL; GARDENIA JASMINOIDES FRUIT; GINGER; 1,2-HEXANEDIOL; NITRIC OXIDE

Active ingredient(s)

Menthol 4.0%

Purpose

Topical analgesic

INDICATIONS AND USAGE

Use(s)

■ temporarily relieves pain associated with minor:

muscle aches

joint pain

backache

strains and sprains

Warnings

■ For external use only

■ Do not use

on wounds or damaged skin

with a heating pad

if you are allergic to menthol or any of the ingredients in this product

■ When using this product

avoid contact with eyes or mucous membranes

do not bandage tightly

use only as directed

keep away from excessive heat

■ Stop use and ask a doctor if rash occurs

■ Keep out of reach of children, If product is swallowed, get medical help or contact a Poison Control Center right away.

■ Keep out of reach of children, If product is swallowed, get medical help or contact a Poison Control Center right away.

Directions

■ adults and children 12 years and older:

apply to affected area not more than 1 to 2 times daily

rub in thoroughly until absorbed

■ children under 12 years of age:

ask a doctor

Other Information

■ Do not store this product in an inappropriate place such as high or low temperatures or under direct sun light

Questions

■ www.kbeone.com

Inactive ingredients

Mineral Oil, Hydrogenated Dicyclopentadiene/Isopentene/Isoprene/Styrene Copolymer, Hydrogenated Styrene/Butadiene Copolymer, Silicate, Ginger, Soil mineral, Styrene Copolymer, Hydrogenated Styrene, Butadiene/Isoprene Copolymer, 1,2-Hexandiol, Lavender Oil, Chamomile Oil, Nitric oxide, Cordyceps Sinensis Extract, Gardenia, MSM